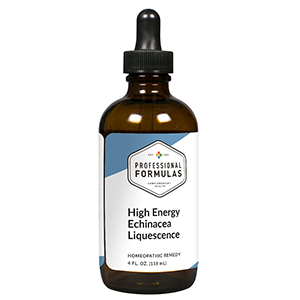 DRUG LABEL: High Energy Echinacea Liquescence
NDC: 63083-3033 | Form: LIQUID
Manufacturer: Professional Complementary Health Formulas
Category: homeopathic | Type: HUMAN OTC DRUG LABEL
Date: 20190815

ACTIVE INGREDIENTS: ECHINACEA ANGUSTIFOLIA WHOLE 1 [hp_X]/118 mL; ECHINACEA PURPUREA WHOLE 1 [hp_X]/118 mL; HYSSOPUS OFFICINALIS WHOLE 6 [hp_X]/118 mL
INACTIVE INGREDIENTS: ALCOHOL; WATER

T33

ACTIVE INGREDIENTS

Echinacea angustifolia 1X, 3X, 6X, 12X, 30X
Echinacea purpurea 1X, 3X, 6X, 12X, 30X
Thymus 6X, 12X

QUESTIONS

Professional Formulas

PO Box 2034 Lake Oswego, OR 97035

INDICATIONS

For the temporary relief of low-grade fever, inflammation, chills, minor muscle aches or pains, exhaustion, or weakness.*

PURPOSE

*Claims based on traditional homeopathic practice, not accepted medical evidence. Not FDA evaluated.

WARNINGS

Persistent symptoms may be a sign of a serious condition. If symptoms persist or are accompanied by a fever, rash, or persistent headache, consult a doctor. Keep out of the reach of children. In case of overdose, get medical help or contact a poison control center right away. If pregnant or breastfeeding, ask a healthcare professional before use.

Keep out of the reach of children.

PREGNANCY OR BREAST FEEDING

If pregnant or breastfeeding, ask a healthcare professional before use.

DIRECTIONS

Place drops under tongue 30 minutes before/after meals. Adults and children 12 years and over: Take one full dropper up to 2 times per day. Consult a physician for use in children under 12 years of age.

OTHER INFORMATION

Tamper resistant. If seal is broken, do not use. After opening, close container tightly and store at room temperature away from heat.

INACTIVE INGREDIENTS

10% ethanol, 8% vegetable glycerin (from soy), 5% cherry extract, purified water.

LABEL

Est 1985

Professional Formulas

Complementary Health

High Energy Echinacea Liquescence

Homeopathic Remedy

4 FL. OZ. (118 mL)